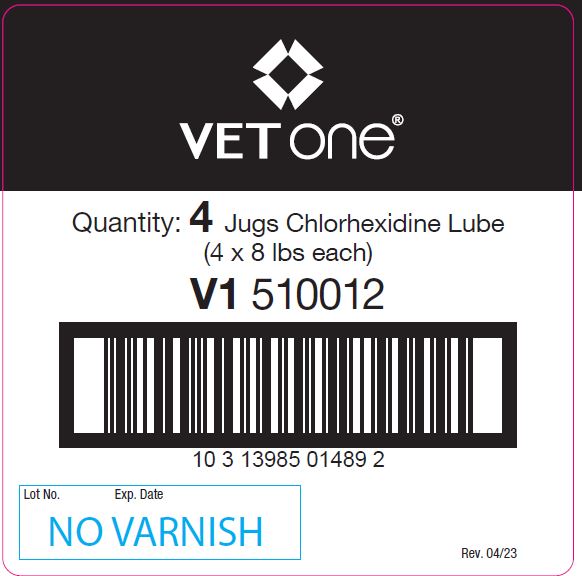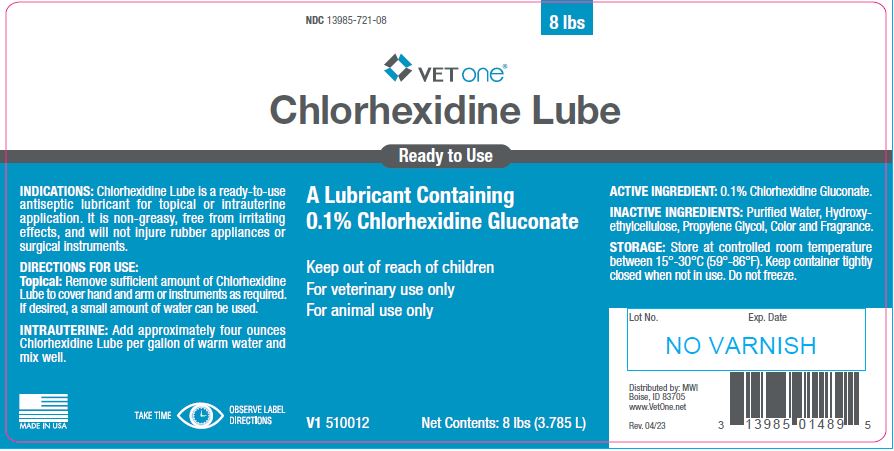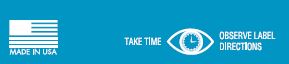 DRUG LABEL: Chlorhexidine Lube
NDC: 13985-721 | Form: JELLY
Manufacturer: MWI/Vet One
Category: animal | Type: OTC ANIMAL DRUG LABEL
Date: 20230518

ACTIVE INGREDIENTS: CHLORHEXIDINE GLUCONATE 5.26 g/1 L

Chlorhexidine Lube

PURPOSE

Ready to Use

A Lubricant Containing 0.1% Chlorhexidine Gluconate

Keep out of reach of children
For veterinary use only
For animal use only

Net Contents:

8 lbs (3.785 L)

INDICATIONS:

Chlorhexidine Lube is a ready-to-use antiseptic lubricant for topical or intrauterine application. It is non-greasy, free from irritating effects, and will not injure rubber appliances or surgical instruments.

DIRECTIONS FOR USE:

Topical: Remove sufficient amount of Chlorhexidine Lube to cover hand and arm or instruments as required. If desired, a small amount of water can be used.

INTRAUTERINE:

Add approximately four ounces Chlorhexidine Lube per gallon of warm water and mix well.

ACTIVE INGREDIENT:

0.1% Chlorhexidine Gluconate.

INACTIVE INGREDIENTS:

Purified Water, Hydroxyethylcellulose, Propylene Glycol, Color and Fragrance.

STORAGE:

Store at controlled room temperature between 15°-30°C (59°-86°F). Keep container tightly closed when not in use. Do not freeze.

INFORMATION FOR OWNERS/CAREGIVERS

Distributed by: MWI
Boise, ID 83705
www.VetOne.net

Rev. 04/23

V1 510012